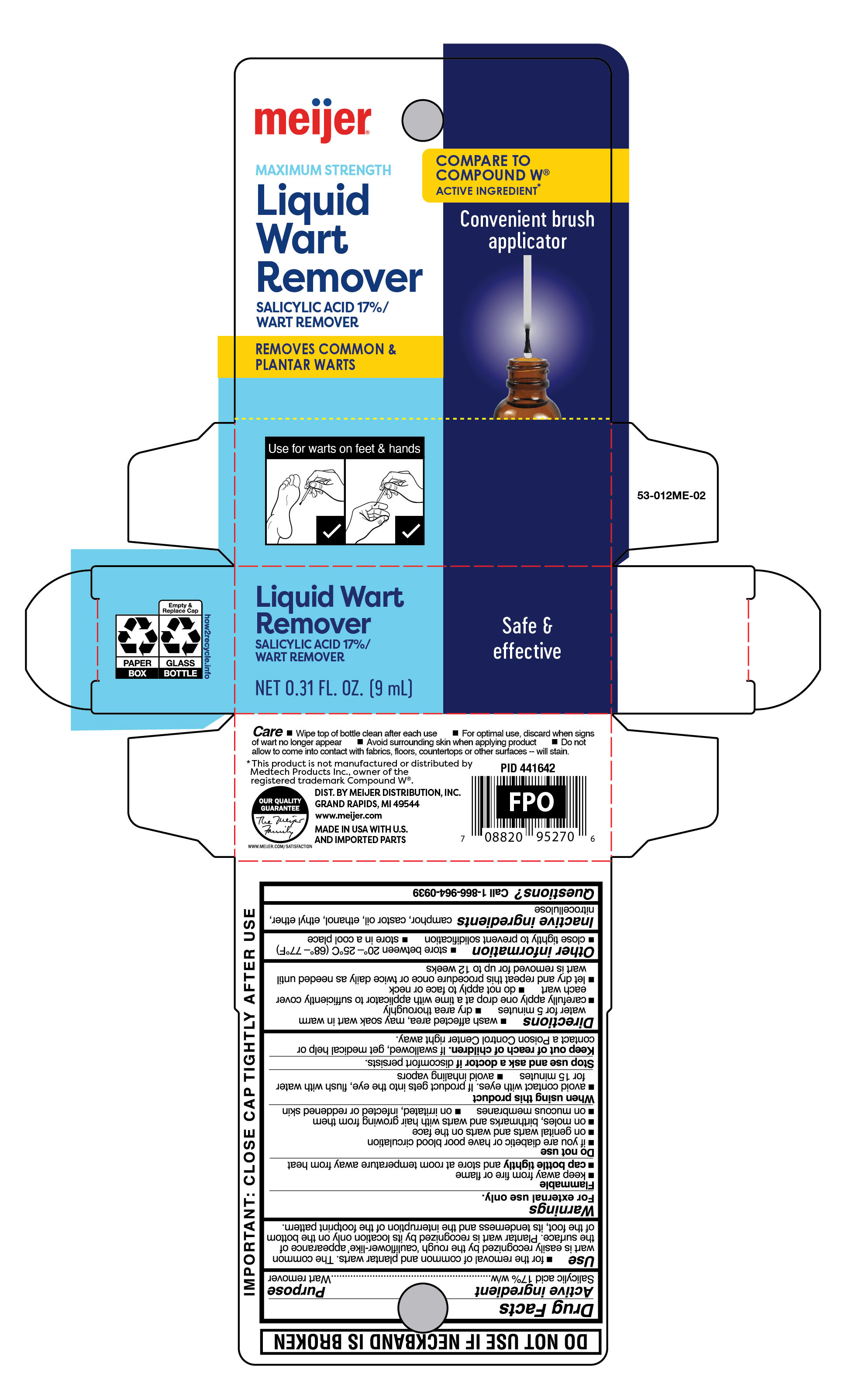 DRUG LABEL: Liquid Wart Remover
NDC: 79481-0614 | Form: LIQUID
Manufacturer: Meijer Distribution Inc
Category: otc | Type: HUMAN OTC DRUG LABEL
Date: 20251007

ACTIVE INGREDIENTS: SALICYLIC ACID 170 mg/1 mL
INACTIVE INGREDIENTS: PYROXYLIN; CAMPHOR (NATURAL); CASTOR OIL

Meijer Liquid Wart Remover

Active ingredient

Salicylic acid 17% w/w

Purpose

Wart remover

Uses

- for the removal of common and plantar warts. The common wart is easily recognized by the rough 'cauliflower-like' appearance of the surface. Plantar wart is recognized by its location only on the bottom of the foot, its tenderness and the interruption of the footprint pattern.

Warnings

For external use only.

Flammable

- keep away from fire or flame
- cap bottle tightly and store at room temerature away from heat

Do not use

- if you are a diabetic or have poor blood circulation, except under the advice and supervision of a doctor or podiatrist
- on genital warts and warts on the face
- on moles, birthmarks and warts with hair growing from them
- on mucous membranes
- on irritated, infected or reddened skin

When using this product

- avoid contact with eyes. If product gets into the eye, flush with water for 15 minutes
- avoid inhaling vapors

Stop use and ask doctor if

discomfort persists.

Keep out of reach of children.

If swallowed, get medical help or contact a Poison Control Center right away.

Directions

- wash affected area, may soak wart in warm water for 5 minutes
- dry area thoroughly
- carefully apply small amount of wart remover with applicator to sufficiently cover each wart
- do not apply to face or neck
- let dry and repeat this procedure once or twice daily as needed until wart is removed for up to 12 weeks

Other information

store between 20° to 25°C (68° to 77°F)

- close tightly to prevent solidification
- store in a cool place

Inactive ingredients

camphor, castor oil, ethanol, ethyl ether, nitrocellulose

Questions?

Call 1-866-964-0939

Principal Display Panel

meijer

liquid

wart remover

Salicylic Acid

Maximum Strength

Removes common & plantar warts

Convenient brush applicator

Safe & effective

NET 0.31 FL OZ (9mL)